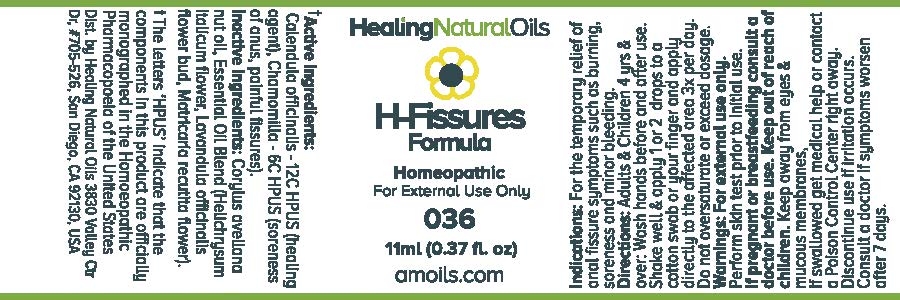 DRUG LABEL: H-Fissures Formula
                
NDC: 61077-036 | Form: OIL
Manufacturer: Healing Natural Oils LLC
Category: homeopathic | Type: HUMAN OTC DRUG LABEL
Date: 20171227

ACTIVE INGREDIENTS: CALENDULA OFFICINALIS FLOWERING TOP 12 [hp_C]/11 mL; MATRICARIA RECUTITA  6 [hp_C]/11 mL
INACTIVE INGREDIENTS: EUROPEAN HAZELNUT OIL; HELICHRYSUM ITALICUM FLOWER; LAVANDULA ANGUSTIFOLIA FLOWER ; CHAMOMILE

Active Ingredients:

Calendula officinalis -12C HPUS
Chamomilla - 6C HPUS

Purpose

Calendula officinalis - 12C HPUS (healing agent),
Chamomilla - 6C HPUS (soreness of anus, painful fissures).

The letters ‘HPUS’ indicate that the components in this product are officially
monographed in the Homoeopathic Pharmacopoeia of the United States

Inactive Ingredients:

Corylus avellana nut oil, Essential Oil Blend (Helichrysum
italicum flower, Lavandula officinalis flower
bud, Matricaria recutita flower)

Indications:

For the temporary relief of anal fissure symptoms such as burning, soreness and minor bleeding.

Directions:

Adults and Children 4 yrs and over: Wash hands before and after use.
Shake well and apply 1 or 2 drops to a cotton swab or your finger and apply directly to the affected area 3x per day.
Do not oversaturate or exceed dosage.

Warnings:

For external use only.
Perform skin test prior to initial use.

PREGNANCY OR BREAST FEEDING

If pregnant or breastfeeding consult a doctor before use.

Keep out of reach of children.

OTHER SAFETY INFORMATION

Keep away from eyes and mucous membranes. If swallowed get medical help or contact a Poison Control
Center right away.

Discontinue use if irritation occurs.

ASK DOCTOR

Consult a doctor if symptoms worsen after 7 days.

DESCRIPTION

Dist. by Healing Natural Oils 3830 Valley Ctr Dr, #705-526, San Diego, CA 92130, USA

PACKAGE LABEL

Healing Natural Oils

H-Fissures

Formula

Homeopathic

For External Use Only

036

11ml (0.37 fl. oz)
amoils.com